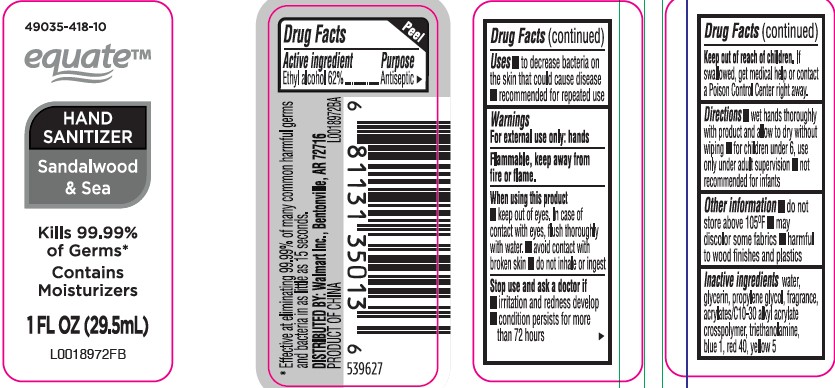 DRUG LABEL: Ethyl alcohol
NDC: 49035-418 | Form: GEL
Manufacturer: Walmart Inc.
Category: otc | Type: HUMAN OTC DRUG LABEL
Date: 20260227

ACTIVE INGREDIENTS: ALCOHOL 62 mL/100 mL
INACTIVE INGREDIENTS: WATER; GLYCERIN; PROPYLENE GLYCOL; CARBOMER INTERPOLYMER TYPE A (ALLYL SUCROSE CROSSLINKED); TROLAMINE; FD&C BLUE NO. 1; FD&C RED NO. 40; FD&C YELLOW NO. 5

Equate 130.000/130AA
Sandalwood + Sea Hand Sanitizer

active ingredient

Ethyl Alcohol 62%

purpose

Antiseptic

uses

- to decrease bacteria on the skin that could cause disease
- recommended for repeated use

Warnings

For external use only: hands

Flammable, keep away from fire or flame.

When using this product

- keep out of eyes. In case of contact with eyes, flush thoroughly with water.
- avoid contact with broken skin
- do ot inhale or ingest

Stop use and ask a doctor if

- irritation and redness develop
- condition persists for more than 72 hours

Keep out of the reach of children.

If swallowed, get medical help or contact a Poison Control Center right away.

Directions

- wet hands thoroughly with product and allow to dry without wiping
- for children under 6, use only under adult supervision
- not recommended for infants

Other information

- do not store above 105°F
- may discolor some fabrics
- harmful to wood finishes and plastics

Inactive ingredients

water, glycerin, propylene glycol, fragrance, acrylates/C10-30 alkyl acrylate crosspolymer, triethanolamine, blue 1, red 40, yellow 5

Claims

*Effective at eliminating 99.99% of many common harmful germs and bacteria in as little as 15 seconds.

Adverse Reactions

DISTRIBUTED BY: Walmart Inc., Bentonville, AR 72716

Product of China

Principal Panel Display

49035-418-10

equate™

HAND SANITIZER

Sandalwood & Sea

Kills 99.99% of Germs*

Contains Moisturizers

1 FL OZ (29.5 mL)